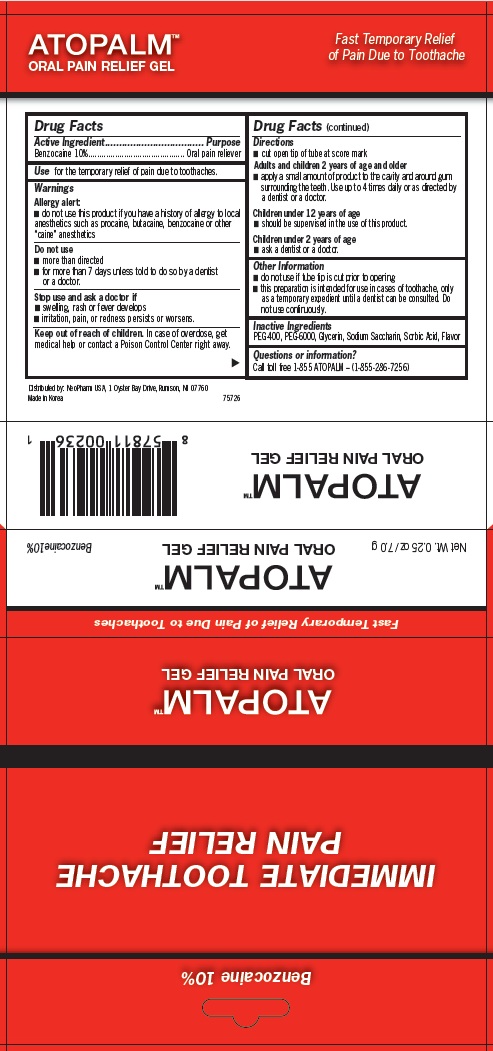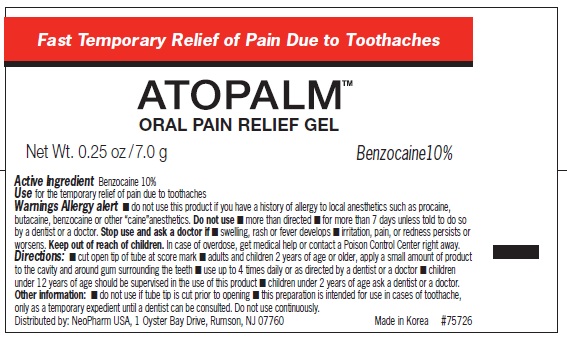 DRUG LABEL: ATOPALM Oral Pain Relief
NDC: 51141-0236 | Form: GEL
Manufacturer: NeoPharm, USA
Category: otc | Type: HUMAN OTC DRUG LABEL
Date: 20120206

ACTIVE INGREDIENTS: BENZOCAINE 10 g/100 g
INACTIVE INGREDIENTS: POLYETHYLENE GLYCOL 400; POLYETHYLENE GLYCOL 6000; GLYCERIN; SACCHARIN SODIUM; SORBIC ACID

ATOPALM Oral Pain Relief Gel

Active Ingredient

Benzocaine 10%

Purpose

Oral Pain Reliever

Use

for the temporary relief of pain due to toothaches.

Warnings

Allergy alert:

- do not use this product if you have a history of allergy to local anesthetics such as procaine, butacaine, benzocaine or other “caine” anesthetics

Do not use

- more than directed
- for more than 7 days unless told to do so by a dentist or a doctor.

Stop use and ask a doctor if

- swelling, rash or fever develops
- irritation, pain, or redness persists or worsens.

Keep out of reach of children.

In case of overdose, get medical help or contact a Poison Control Center right away.

Directions

- cut open tip of tube at score mark

Adults and children 2 years of age and older

- apply a small amount of product to the cavity and around gum surrounding the teeth. Use up to 4 times daily or as directed by a dentist or a doctor.

Children under 12 years of age

- should be supervised in the use of this product.

Children under 2 years of age

- ask a dentist or a doctor.

Other information

- do not use if tube tip is cut prior to opening
- this preparation is intended for use in cases of toothache, only as a temporary expedient until a dentist can be consulted. Do not use continuously.

Inactive Ingredients

PEG-400, PEG-6000, Glycerin, Sodium Saccharin, Sorbic Acid, Flavor

Questions or information?

Call toll free 1-855 ATOPALM – (1-855-286-7256)

Labeling Information

ATOPALM Oral Pain Relief Gel

Fast Temporary Relief of Pain Due to Toothache

Benzocaine 10%

Distributed by: NeoPharm USA, 1 Oyster Bay Drive, Rumson, NJ 07760
Made in Korea